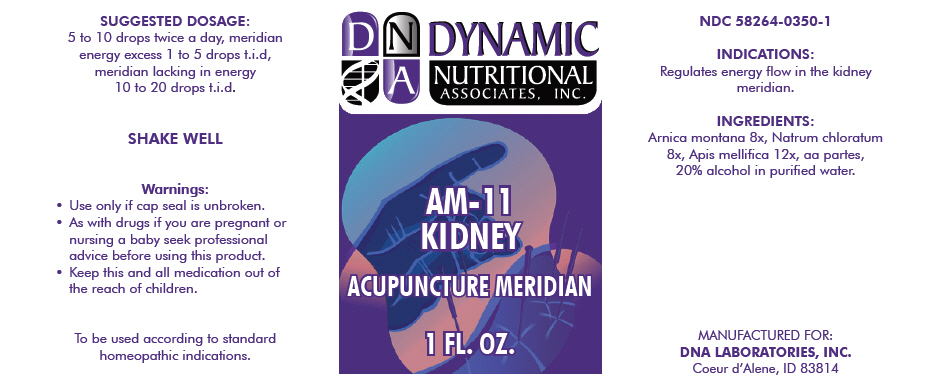 DRUG LABEL: AM-11
NDC: 58264-0350 | Form: SOLUTION
Manufacturer: DNA Labs, Inc.
Category: homeopathic | Type: HUMAN OTC DRUG LABEL
Date: 20250109

ACTIVE INGREDIENTS: ARNICA MONTANA 8 [hp_X]/1 mL; SODIUM CHLORIDE 8 [hp_X]/1 mL; APIS MELLIFERA 12 [hp_X]/1 mL
INACTIVE INGREDIENTS: ALCOHOL; WATER

AM-11

NDC 58264-0350-1

INDICATIONS AND USAGE

INDICATIONS

Regulates energy flow in the kidney meridian.

INGREDIENTS

INACTIVE INGREDIENT

Arnica montana 8x, Natrum chloratum 8x, Apis mellifica 12x, aa partes, 20% alcohol in purified water.

SUGGESTED DOSAGE

5 to 10 drops twice a day, meridian energy excess 1 to 5 drops t.i.d, meridian lacking in energy 10 to 20 drops t.i.d.

STORAGE AND HANDLING

SHAKE WELL

Warnings

- Use only if cap seal is unbroken.

PREGNANCY OR BREAST FEEDING

- As with drugs if you are pregnant or nursing a baby seek professional advice before using this product.

KEEP OUT OF REACH OF CHILDREN

- Keep this and all medication out of the reach of children.

To be used according to standard homeopathic indications.

PRINCIPAL DISPLAY PANEL - 1 FL. OZ. Bottle Label

DYNAMIC
NUTRITIONAL
ASSOCIATES, INC.

AM-11
KIDNEY

ACUPUNCTURE MERIDIAN

1 FL. OZ.